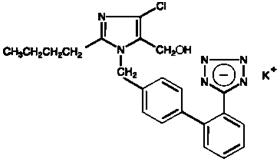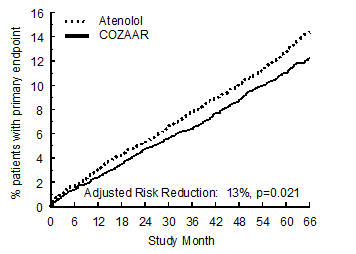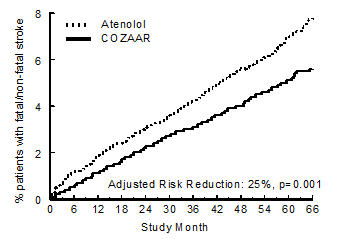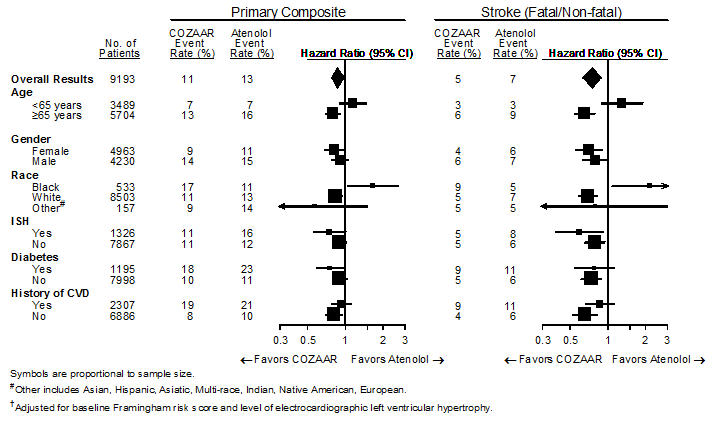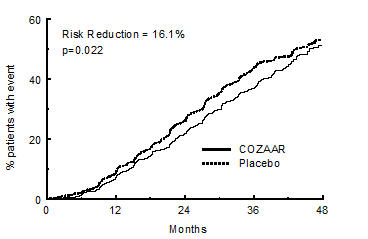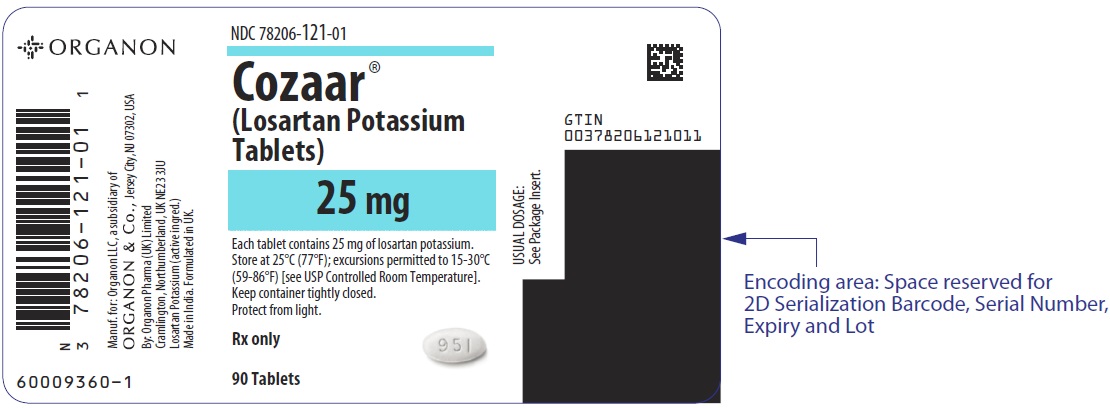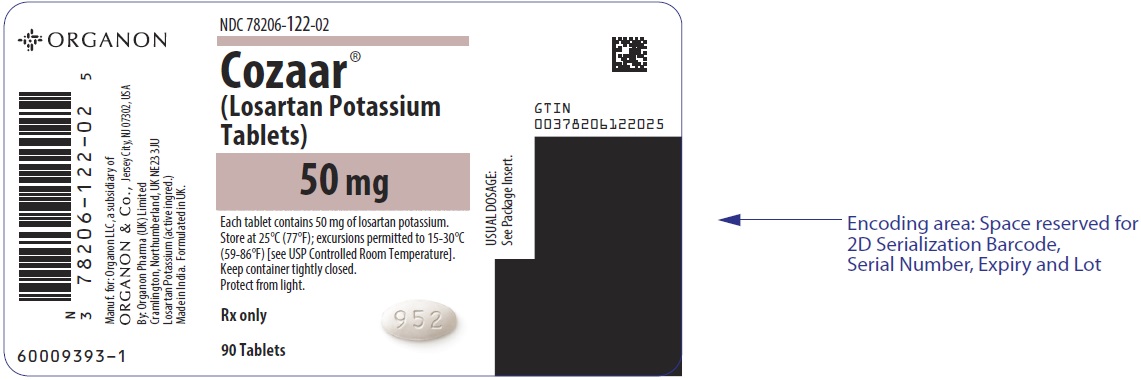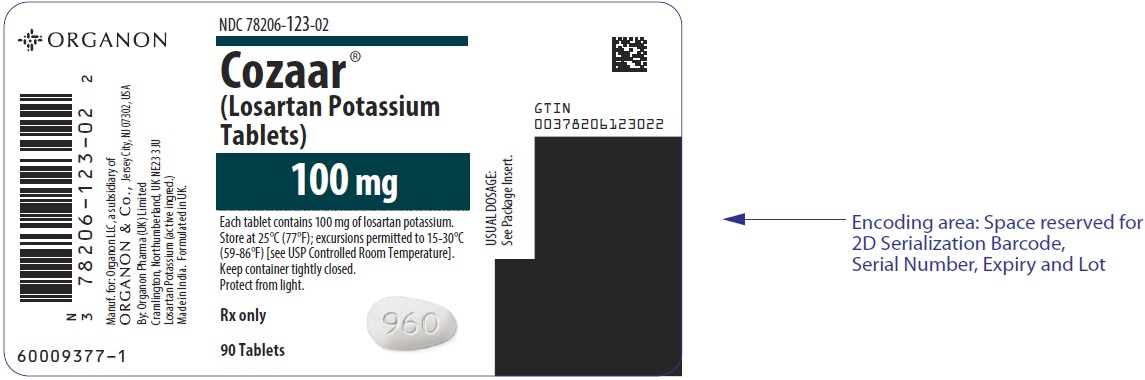 DRUG LABEL: COZAAR
NDC: 78206-121 | Form: TABLET, FILM COATED
Manufacturer: Organon LLC
Category: prescription | Type: HUMAN PRESCRIPTION DRUG LABEL
Date: 20260120

ACTIVE INGREDIENTS: losartan potassium 25 mg/1 1
INACTIVE INGREDIENTS: MICROCRYSTALLINE CELLULOSE; LACTOSE MONOHYDRATE; STARCH, CORN; MAGNESIUM STEARATE; HYDROXYPROPYL CELLULOSE (1600000 WAMW); HYPROMELLOSE, UNSPECIFIED; TITANIUM DIOXIDE; CARNAUBA WAX

HIGHLIGHTS OF PRESCRIBING INFORMATION

These highlights do not include all the information needed to use COZAAR safely and effectively. See full prescribing information for COZAAR.
COZAAR® (losartan potassium) tablets, for oral use
Initial U.S. Approval: 1995

WARNING: FETAL TOXICITY

See full prescribing information for complete boxed warning.

When pregnancy is detected, discontinue COZAAR as soon as possible. Drugs that act directly on the renin-angiotensin system can cause injury and death to the developing fetus. (5.1)

1 INDICATIONS AND USAGE

COZAAR is an angiotensin II receptor blocker (ARB) indicated for:

- Treatment of hypertension, to lower blood pressure in adults and children greater than 6 years old. Lowering blood pressure reduces the risk of fatal and nonfatal cardiovascular events, primarily strokes and myocardial infarctions. (1.1)
- Reduction of the risk of stroke in patients with hypertension and left ventricular hypertrophy. There is evidence that this benefit does not apply to Black patients. (1.2)
- Treatment of diabetic nephropathy with an elevated serum creatinine and proteinuria in patients with type 2 diabetes and a history of hypertension. (1.3)

2 DOSAGE AND ADMINISTRATION

Hypertension

- Usual adult dose: 50 mg once daily. (2.1)
- Usual pediatric starting dose: 0.7 mg per kg once daily (up to 50 mg). (2.1)

Hypertensive Patients with Left Ventricular Hypertrophy

- Usual starting dose: 50 mg once daily. (2.2)
- Add hydrochlorothiazide 12.5 mg and/or increase COZAAR to 100 mg followed by an increase to hydrochlorothiazide 25 mg if further blood pressure response is needed. (2.2, 14.2)

Nephropathy in Type 2 Diabetic Patients

- Usual dose: 50 mg once daily. (2.3)
- Increase dose to 100 mg once daily if further blood pressure response is needed. (2.3)

3 DOSAGE FORMS AND STRENGTHS

Tablets: 25 mg; 50 mg; and 100 mg. (3)

4 CONTRAINDICATIONS

- Hypersensitivity to any component. (4)
- Coadministration with aliskiren in patients with diabetes. (4)

5 WARNINGS AND PRECAUTIONS

- Hypotension: Correct volume or salt depletion prior to administration of COZAAR. (5.2)
- Monitor renal function and potassium in susceptible patients. (5.3, 5.4)

6 ADVERSE REACTIONS

Most common adverse reactions (incidence ≥2% and greater than placebo) are: dizziness, upper respiratory infection, nasal congestion, and back pain. (6.1)
To report SUSPECTED ADVERSE REACTIONS, contact Organon LLC, a subsidiary of Organon & Co., at 1-844-674-3200 or FDA at 1-800-FDA-1088 or www.fda.gov/medwatch.

7 DRUG INTERACTIONS

- Agents Increasing Serum Potassium: Risk of hyperkalemia. (7.1)
- Lithium: Risk of lithium toxicity. (7.2)
- NSAIDs: Increased risk of renal impairment and reduced diuretic, natriuretic, and antihypertensive effects. (7.3)
- Dual Inhibition of the Renin-Angiotensin System: Increased risk of renal impairment, hypotension, syncope, and hyperkalemia. (7.4)

8 USE IN SPECIFIC POPULATIONS

- COZAAR is not recommended in pediatric patients less than 6 years of age or in pediatric patients with glomerular filtration rate less than 30 mL/min/1.73 m^2. (2.1, 8.4)
- Hepatic Impairment: Recommended starting dose 25 mg once daily. (2.4, 8.8, 12.3)

FULL PRESCRIBING INFORMATION

WARNING: FETAL TOXICITY

When pregnancy is detected, discontinue COZAAR as soon as possible. Drugs that act directly on the renin-angiotensin system can cause injury and death to the developing fetus [see Warnings and Precautions (5.1)].

1 INDICATIONS AND USAGE

1.1 Hypertension

COZAAR® is indicated for the treatment of hypertension in adults and pediatric patients 6 years of age and older, to lower blood pressure. Lowering blood pressure lowers the risk of fatal and nonfatal cardiovascular (CV) events, primarily strokes and myocardial infarction. These benefits have been seen in controlled trials of antihypertensive drugs from a wide variety of pharmacologic classes including losartan.

Control of high blood pressure should be part of comprehensive cardiovascular risk management, including, as appropriate, lipid control, diabetes management, antithrombotic therapy, smoking cessation, exercise, and limited sodium intake. Many patients will require more than 1 drug to achieve blood pressure goals. For specific advice on goals and management, see published guidelines, such as those of the National High Blood Pressure Education Program's Joint National Committee on Prevention, Detection, Evaluation, and Treatment of High Blood Pressure (JNC).

Numerous antihypertensive drugs, from a variety of pharmacologic classes and with different mechanisms of action, have been shown in randomized controlled trials to reduce cardiovascular morbidity and mortality, and it can be concluded that it is blood pressure reduction, and not some other pharmacologic property of the drugs, that is largely responsible for those benefits. The largest and most consistent cardiovascular outcome benefit has been a reduction in the risk of stroke, but reductions in myocardial infarction and cardiovascular mortality also have been seen regularly.

Elevated systolic or diastolic pressure causes increased cardiovascular risk, and the absolute risk increase per mmHg is greater at higher blood pressures, so that even modest reductions of severe hypertension can provide substantial benefit. Relative risk reduction from blood pressure reduction is similar across populations with varying absolute risk, so the absolute benefit is greater in patients who are at higher risk independent of their hypertension (for example, patients with diabetes or hyperlipidemia), and such patients would be expected to benefit from more aggressive treatment to a lower blood pressure goal.

Some antihypertensive drugs have smaller blood pressure effects (as monotherapy) in Black patients, and many antihypertensive drugs have additional approved indications and effects (e.g., on angina, heart failure, or diabetic kidney disease). These considerations may guide selection of therapy.

COZAAR may be administered with other antihypertensive agents.

1.2 Hypertensive Patients with Left Ventricular Hypertrophy

COZAAR is indicated to reduce the risk of stroke in patients with hypertension and left ventricular hypertrophy, but there is evidence that this benefit does not apply to Black patients [see Use in Specific Populations (8.6) and Clinical Pharmacology (12.3)].

1.3 Nephropathy in Type 2 Diabetic Patients

COZAAR is indicated for the treatment of diabetic nephropathy with an elevated serum creatinine and proteinuria (urinary albumin to creatinine ratio ≥300 mg/g) in patients with type 2 diabetes and a history of hypertension. In this population, COZAAR reduces the rate of progression of nephropathy as measured by the occurrence of doubling of serum creatinine or end stage renal disease (need for dialysis or renal transplantation) [see Clinical Studies (14.3)].

2 DOSAGE AND ADMINISTRATION

2.1 Hypertension

Adult Hypertension

The usual starting dose of COZAAR is 50 mg once daily. The dosage can be increased to a maximum dose of 100 mg once daily as needed to control blood pressure [see Clinical Studies (14.1)]. A starting dose of 25 mg is recommended for patients with possible intravascular depletion (e.g., on diuretic therapy).

Pediatric Hypertension

The usual recommended starting dose is 0.7 mg per kg once daily (up to 50 mg total) administered as a tablet or a suspension [see Dosage and Administration (2.5)]. Dosage should be adjusted according to blood pressure response. Doses above 1.4 mg per kg (or in excess of 100 mg) daily have not been studied in pediatric patients [see Clinical Pharmacology (12.3), Clinical Studies (14.1), and Warnings and Precautions (5.2)].

COZAAR is not recommended in pediatric patients less than 6 years of age or in pediatric patients with estimated glomerular filtration rate less than 30 mL/min/1.73 m^2 [see Use in Specific Populations (8.4), Clinical Pharmacology (12.3), and Clinical Studies (14)].

2.2 Hypertensive Patients with Left Ventricular Hypertrophy

The usual starting dose is 50 mg of COZAAR once daily. Hydrochlorothiazide 12.5 mg daily should be added and/or the dose of COZAAR should be increased to 100 mg once daily followed by an increase in hydrochlorothiazide to 25 mg once daily based on blood pressure response [see Clinical Studies (14.2)].

2.3 Nephropathy in Type 2 Diabetic Patients

The usual starting dose is 50 mg once daily. The dose should be increased to 100 mg once daily based on blood pressure response [see Clinical Studies (14.3)].

2.4 Dosage Modifications in Patients with Hepatic Impairment

In patients with mild-to-moderate hepatic impairment the recommended starting dose of COZAAR is 25 mg once daily. COZAAR has not been studied in patients with severe hepatic impairment [see Use in Specific Populations (8.8) and Clinical Pharmacology (12.3)].

2.5 Preparation of Suspension (for 200 mL of a 2.5 mg/mL suspension)

Add 10 mL of Purified Water USP to an 8 ounce (240 mL) amber polyethylene terephthalate (PET) bottle containing ten 50 mg COZAAR tablets. Immediately shake for at least 2 minutes. Let the concentrate stand for 1 hour and then shake for 1 minute to disperse the tablet contents. Separately prepare a 50/50 volumetric mixture of Ora-Plus™ and Ora-Sweet SF™. Add 190 mL of the 50/50 Ora-Plus™/Ora-Sweet SF™ mixture to the tablet and water slurry in the PET bottle and shake for 1 minute to disperse the ingredients. The suspension should be refrigerated at 2-8°C (36-46°F) and can be stored for up to 4 weeks. Shake the suspension prior to each use and return promptly to the refrigerator.

3 DOSAGE FORMS AND STRENGTHS

- COZAAR, 25 mg, are white, oval, film-coated tablets with code 951 on one side.
- COZAAR, 50 mg, are white, oval, film-coated tablets with code 952 on one side and scored on the other.
- COZAAR, 100 mg, are white, teardrop-shaped, film-coated tablets with code 960 on one side.

4 CONTRAINDICATIONS

COZAAR is contraindicated:

- In patients who are hypersensitive to any component of this product.
- For coadministration with aliskiren in patients with diabetes.

5 WARNINGS AND PRECAUTIONS

5.1 Fetal Toxicity

COZAAR can cause fetal harm when administered to a pregnant woman. Use of drugs that act on the renin-angiotensin system during the second and third trimesters of pregnancy reduces fetal renal function and increases fetal and neonatal morbidity and death. Resulting oligohydramnios can be associated with fetal lung hypoplasia and skeletal deformations. Potential neonatal adverse effects include skull hypoplasia, anuria, hypotension, renal failure, and death. When pregnancy is detected, discontinue COZAAR as soon as possible [see Use in Specific Populations (8.1)].

5.2 Hypotension in Volume- or Salt-Depleted Patients

In patients with an activated renin-angiotensin system, such as volume- or salt-depleted patients (e.g., those being treated with high doses of diuretics), symptomatic hypotension may occur after initiation of treatment with COZAAR. Correct volume or salt depletion prior to administration of COZAAR [see Dosage and Administration (2.1)].

5.3 Renal Function Deterioration

Changes in renal function including acute renal failure can be caused by drugs that inhibit the renin-angiotensin system and by diuretics. Patients whose renal function may depend in part on the activity of the renin-angiotensin system (e.g., patients with renal artery stenosis, chronic kidney disease, severe congestive heart failure, or volume depletion) may be at particular risk of developing acute renal failure on COZAAR. Monitor renal function periodically in these patients. Consider withholding or discontinuing therapy in patients who develop a clinically significant decrease in renal function on COZAAR [see Drug Interactions (7.3) and Use in Specific Populations (8.7)].

5.4 Hyperkalemia

Monitor serum potassium periodically and treat appropriately. Dosage reduction or discontinuation of COZAAR may be required [see Adverse Reactions (6.1)].

Concomitant use of other drugs that may increase serum potassium may lead to hyperkalemia [see Drug Interactions (7.1)].

6 ADVERSE REACTIONS

6.1 Clinical Trials Experience

Because clinical trials are conducted under widely varying conditions, adverse reaction rates observed in the clinical trials of a drug cannot be directly compared to rates in the clinical trials of another drug and may not reflect the rates observed in practice.

Hypertension

COZAAR has been evaluated for safety in more than 3300 adult patients treated for essential hypertension and 4058 patients/subjects overall. Over 1200 patients were treated for over 6 months and more than 800 for over one year.

Treatment with COZAAR was well-tolerated with an overall incidence of adverse events similar to that of placebo. In controlled clinical trials, discontinuation of therapy for adverse events occurred in 2.3% of patients treated with COZAAR and 3.7% of patients given placebo. In 4 clinical trials involving over 1000 patients on various doses (10-150 mg) of losartan potassium and over 300 patients given placebo, the adverse events that occurred in ≥2% of patients treated with COZAAR and more commonly than placebo were: dizziness (3% vs. 2%), upper respiratory infection (8% vs. 7%), nasal congestion (2% vs. 1%), and back pain (2% vs. 1%).

The following less common adverse reactions have been reported:

Blood and lymphatic system disorders: Anemia.

Psychiatric disorders: Depression.

Nervous system disorders: Somnolence, headache, sleep disorders, paresthesia, migraine.

Ear and labyrinth disorders: Vertigo, tinnitus.

Cardiac disorders: Palpitations, syncope, atrial fibrillation, CVA.

Respiratory, thoracic and mediastinal disorders: Dyspnea.

Gastrointestinal disorders: Abdominal pain, constipation, nausea, vomiting.

Skin and subcutaneous tissue disorders: Urticaria, pruritus, rash, photosensitivity.

Musculoskeletal and connective tissue disorders: Myalgia, arthralgia.

Reproductive system and breast disorders: Impotence.

General disorders and administration site conditions: Edema.

Cough

Persistent dry cough (with an incidence of a few percent) has been associated with ACE-inhibitor use and in practice can be a cause of discontinuation of ACE-inhibitor therapy. Two prospective, parallel-group, double-blind, randomized, controlled trials were conducted to assess the effects of losartan on the incidence of cough in hypertensive patients who had experienced cough while receiving ACE-inhibitor therapy. Patients who had typical ACE-inhibitor cough when challenged with lisinopril, whose cough disappeared on placebo, were randomized to losartan 50 mg, lisinopril 20 mg, or either placebo (one study, n=97) or 25 mg hydrochlorothiazide (n=135). The double-blind treatment period lasted up to 8 weeks. The incidence of cough is shown in Table 1 below.

Table 1
Study 1 [Demographics = (89% Caucasian, 64% female)] | HCTZ | Losartan | Lisinopril
Cough | 25% | 17% | 69%
Study 2 [Demographics = (90% Caucasian, 51% female)] | Placebo | Losartan | Lisinopril
Cough | 35% | 29% | 62%

These studies demonstrate that the incidence of cough associated with losartan therapy, in a population that all had cough associated with ACE-inhibitor therapy, is similar to that associated with hydrochlorothiazide or placebo therapy.

Cases of cough, including positive re-challenges, have been reported with the use of losartan in postmarketing experience.

Hypertensive Patients with Left Ventricular Hypertrophy

In the Losartan Intervention for Endpoint (LIFE) study, adverse reactions with COZAAR were similar to those reported previously for patients with hypertension.

Nephropathy in Type 2 Diabetic Patients

In the Reduction of Endpoints in NIDDM with the Angiotensin II Receptor Antagonist Losartan (RENAAL) study involving 1513 patients treated with COZAAR or placebo, the overall incidences of reported adverse events were similar for the two groups. Discontinuations of COZAAR because of side effects were similar to placebo (19% for COZAAR, 24% for placebo). The adverse events, regardless of drug relationship, reported with an incidence of ≥4% of patients treated with COZAAR and occurring with ≥2% difference in the losartan group vs. placebo on a background of conventional antihypertensive therapy, were asthenia/fatigue, chest pain, hypotension, orthostatic hypotension, diarrhea, anemia, hyperkalemia, hypoglycemia, back pain, muscular weakness, and urinary tract infection.

6.2 Postmarketing Experience

The following additional adverse reactions have been reported in postmarketing experience with COZAAR. Because these reactions are reported voluntarily from a population of uncertain size, it is not always possible to estimate their frequency reliably or to establish a causal relationship to drug exposure:

Digestive: Hepatitis.

General Disorders and Administration Site Conditions: Malaise.

Hematologic: Thrombocytopenia.

Hypersensitivity: Angioedema, including swelling of the larynx and glottis, causing airway obstruction and/or swelling of the face, lips, pharynx, tongue, and/or swelling of the intestine has been reported; some of these patients previously experienced angioedema with other drugs including ACE inhibitors. Vasculitis, including Henoch-Schönlein purpura, has been reported. Anaphylactic reactions have been reported.

Metabolic and Nutrition: Hyponatremia.

Musculoskeletal: Rhabdomyolysis.

Nervous System Disorders: Dysgeusia.

Skin: Erythroderma.

7 DRUG INTERACTIONS

7.1 Agents Increasing Serum Potassium

Coadministration of losartan with other drugs that raise serum potassium levels may result in hyperkalemia. Monitor serum potassium in such patients.

7.2 Lithium

Increases in serum lithium concentrations and lithium toxicity have been reported during concomitant administration of lithium with angiotensin II receptor antagonists. Monitor serum lithium levels during concomitant use.

7.3 Non-Steroidal Anti-Inflammatory Drugs (NSAIDs) Including Selective Cyclooxygenase-2 Inhibitors (COX-2 Inhibitors)

In patients who are elderly, volume-depleted (including those on diuretic therapy), or with compromised renal function, coadministration of NSAIDs, including selective COX-2 inhibitors, with angiotensin II receptor antagonists (including losartan) may result in deterioration of renal function, including possible acute renal failure. These effects are usually reversible. Monitor renal function periodically in patients receiving losartan and NSAID therapy.

The antihypertensive effect of angiotensin II receptor antagonists, including losartan, may be attenuated by NSAIDs, including selective COX-2 inhibitors.

7.4 Dual Blockade of the Renin-Angiotensin System (RAS)

Dual blockade of the RAS with angiotensin receptor blockers, ACE inhibitors, or aliskiren is associated with increased risks of hypotension, syncope, hyperkalemia, and changes in renal function (including acute renal failure) compared to monotherapy.

The Veterans Affairs Nephropathy in Diabetes (VA NEPHRON-D) trial enrolled 1448 patients with type 2 diabetes, elevated urinary-albumin-to-creatinine ratio, and decreased estimated glomerular filtration rate (GFR 30 to 89.9 mL/min), randomized them to lisinopril or placebo on a background of losartan therapy and followed them for a median of 2.2 years. Patients receiving the combination of losartan and lisinopril did not obtain any additional benefit compared to monotherapy for the combined endpoint of decline in GFR, end stage renal disease, or death, but experienced an increased incidence of hyperkalemia and acute kidney injury compared with the monotherapy group.

In most patients no benefit has been associated with using two RAS inhibitors concomitantly. In general, avoid combined use of RAS inhibitors. Closely monitor blood pressure, renal function, and electrolytes in patients on COZAAR and other agents that affect the RAS.

Do not coadminister aliskiren with COZAAR in patients with diabetes. Avoid use of aliskiren with COZAAR in patients with renal impairment (GFR <60 mL/min).

8 USE IN SPECIFIC POPULATIONS

8.1 Pregnancy

TERATOGENIC EFFECTS

Risk Summary

COZAAR can cause fetal harm when administered to a pregnant woman. Use of drugs that act on the renin-angiotensin system during the second and third trimesters of pregnancy reduces fetal renal function and increases fetal and neonatal morbidity and death. Most epidemiologic studies examining fetal abnormalities after exposure to antihypertensive use in the first trimester have not distinguished drugs affecting the renin-angiotensin system from other antihypertensive agents. When pregnancy is detected, discontinue COZAAR as soon as possible (see Clinical Considerations).

The estimated background risk of major birth defects and miscarriage for the indicated population is unknown. All pregnancies have a background risk of birth defect, loss, or other adverse outcomes. In the U.S. general population, the estimated background risk of major birth defects and miscarriage in clinically recognized pregnancies is 2% to 4% and 15% to 20%, respectively.

Clinical Considerations

Disease-associated Maternal and/or Embryo/Fetal Risk

Hypertension in pregnancy increases the maternal risk for pre-eclampsia, gestational diabetes, premature delivery, and delivery complications (e.g., need for cesarean section, post-partum hemorrhage). Hypertension increases the fetal risk for intrauterine growth restriction and intrauterine death. Pregnant women with hypertension should be carefully monitored and managed accordingly.

Fetal/Neonatal Adverse Reactions

Oligohydramnios in pregnant women who use drugs affecting the renin-angiotensin system in the second and third trimesters of pregnancy can result in the following: reduced fetal renal function leading to anuria and renal failure, fetal lung hypoplasia, skeletal deformations, including skull hypoplasia, hypotension, and death. In the unusual case that there is no appropriate alternative to therapy with drugs affecting the renin-angiotensin system for a particular patient, apprise the mother of the potential risk to the fetus.

In patients taking COZAAR during pregnancy, perform serial ultrasound examinations to assess the intra-amniotic environment. Fetal testing may be appropriate, based on the week of gestation. If oligohydramnios is observed, discontinue COZAAR, unless it is considered lifesaving for the mother. Patients and physicians should be aware, however, that oligohydramnios may not appear until after the fetus has sustained irreversible injury.

Closely observe neonates with histories of in utero exposure to COZAAR for hypotension, oliguria, and hyperkalemia. In neonates with a history of in utero exposure to COZAAR, if oliguria or hypotension occurs, support blood pressure and renal perfusion. Exchange transfusions or dialysis may be required as a means of reversing hypotension and replacing renal function.

Data

Animal Data

Losartan potassium was administered orally to rats during the period of late gestation through lactation (Gestation Day 15 through Lactation Day 20) at doses of 10, 25, and 100 mg/kg/day. Losartan potassium has been shown to produce adverse effects in rat fetuses and neonates, including decreased body weight, delayed physical and behavioral development, mortality and renal toxicity. With the exception of neonatal weight gain (which was affected at doses as low as 10 mg/kg/day), doses associated with these effects exceeded 25 mg/kg/day (approximately three times the maximum recommended human dose of 100 mg on a mg/m^2 basis). These findings are attributed to drug exposure in late gestation and during lactation. Significant levels of losartan and its active metabolite were shown to be present in rat fetal plasma during late gestation and in rat milk.

8.2 Lactation

Risk Summary

It is not known whether losartan is excreted in human milk, but significant levels of losartan and its active metabolite were shown to be present in rat milk. Because of the potential for adverse effects on the nursing infant, a decision should be made whether to discontinue nursing or discontinue the drug, taking into account the importance of the drug to the mother.

8.4 Pediatric Use

Antihypertensive effects of COZAAR have been established in hypertensive pediatric patients aged 6 to 16 years. Safety and effectiveness have not been established in pediatric patients under the age of 6 or in pediatric patients with glomerular filtration rate <30 mL/min/1.73 m^2 [see Dosage and Administration (2.1), Clinical Pharmacology (12.3), and Clinical Studies (14.1)].

8.5 Geriatric Use

Of the total number of patients receiving COZAAR in controlled clinical studies for hypertension, 391 patients (19%) were 65 years and over, while 37 patients (2%) were 75 years and over. In a controlled clinical study for renal protection in type 2 diabetic patients with proteinuria, 248 patients (33%) were 65 years and over. In a controlled clinical study for the reduction in the combined risk of cardiovascular death, stroke and myocardial infarction in hypertensive patients with left ventricular hypertrophy, 2857 patients (62%) were 65 years and over, while 808 patients (18%) were 75 years and over. No overall differences in effectiveness or safety were observed between these patients and younger patients, but greater sensitivity of some older individuals cannot be ruled out.

8.6 Race

In the LIFE study, Black patients with hypertension and left ventricular hypertrophy treated with atenolol were at lower risk of experiencing the primary composite endpoint compared with Black patients treated with COZAAR (both cotreated with hydrochlorothiazide in the majority of patients). The primary endpoint was the first occurrence of stroke, myocardial infarction or cardiovascular death, analyzed using an intention-to-treat (ITT) approach. In the subgroup of Black patients (n=533, 6% of the LIFE study patients), there were 29 primary endpoints among 263 patients on atenolol (11%, 26 per 1000 patient-years) and 46 primary endpoints among 270 patients (17%, 42 per 1000 patient-years) on COZAAR. This finding could not be explained on the basis of differences in the populations other than race or on any imbalances between treatment groups. In addition, blood pressure reductions in both treatment groups were consistent between Black and non-Black patients. Given the difficulty in interpreting subset differences in large trials, it cannot be known whether the observed difference is the result of chance. However, the LIFE study provides no evidence that the benefits of COZAAR on reducing the risk of cardiovascular events in hypertensive patients with left ventricular hypertrophy apply to Black patients [see Clinical Studies (14.2)].

8.7 Renal Impairment

Patients with renal insufficiency have elevated plasma concentrations of losartan and its active metabolite compared to subjects with normal renal function. No dose adjustment is necessary in patients with renal impairment unless a patient with renal impairment is also volume depleted [see Dosage and Administration (2.3), Warnings and Precautions (5.3) and Clinical Pharmacology (12.3)].

8.8 Hepatic Impairment

The recommended starting dose of COZAAR is 25 mg in patients with mild-to-moderate hepatic impairment. Following oral administration in patients with mild-to-moderate hepatic impairment, plasma concentrations of losartan and its active metabolite were, respectively, 5 times and 1.7 times those seen in healthy volunteers. COZAAR has not been studied in patients with severe hepatic impairment [see Dosage and Administration (2.4) and Clinical Pharmacology (12.3)].

10 OVERDOSAGE

Significant lethality was observed in mice and rats after oral administration of 1000 mg/kg and 2000 mg/kg, respectively, about 44 and 170 times the maximum recommended human dose on a mg/m^2 basis.

Limited data are available in regard to overdosage in humans. The most likely manifestation of overdosage would be hypotension and tachycardia; bradycardia could occur from parasympathetic (vagal) stimulation. If symptomatic hypotension should occur, supportive treatment should be instituted.

Neither losartan nor its active metabolite can be removed by hemodialysis.

11 DESCRIPTION

COZAAR (losartan potassium) is an angiotensin II receptor blocker acting on the AT1 receptor subtype. Losartan potassium, a non-peptide molecule, is chemically described as 2-butyl-4-chloro-1-[p-(o-1H-tetrazol-5-ylphenyl)benzyl]imidazole-5-methanol monopotassium salt.

Its empirical formula is C22H22ClKN6O, and its structural formula is:

Losartan potassium is a white to off-white free-flowing crystalline powder with a molecular weight of 461.01. It is freely soluble in water, soluble in alcohols, and slightly soluble in common organic solvents, such as acetonitrile and methyl ethyl ketone. Oxidation of the 5-hydroxymethyl group on the imidazole ring results in the active metabolite of losartan.

COZAAR is available as tablets for oral administration containing either 25 mg, 50 mg or 100 mg of losartan potassium and the following inactive ingredients: microcrystalline cellulose, lactose hydrous, pregelatinized starch, magnesium stearate, hydroxypropyl cellulose, hypromellose, and titanium dioxide.

COZAAR 25 mg, 50 mg and 100 mg tablets contain potassium in the following amounts: 2.12 mg (0.054 mEq), 4.24 mg (0.108 mEq) and 8.48 mg (0.216 mEq), respectively. COZAAR 25 mg, COZAAR 50 mg, and COZAAR 100 mg may also contain carnauba wax.

12 CLINICAL PHARMACOLOGY

12.1 Mechanism of Action

Angiotensin II [formed from angiotensin I in a reaction catalyzed by angiotensin converting enzyme (ACE, kininase II)] is a potent vasoconstrictor, the primary vasoactive hormone of the renin-angiotensin system, and an important component in the pathophysiology of hypertension. It also stimulates aldosterone secretion by the adrenal cortex. Losartan and its principal active metabolite block the vasoconstrictor and aldosterone-secreting effects of angiotensin II by selectively blocking the binding of angiotensin II to the AT1 receptor found in many tissues, (e.g., vascular smooth muscle, adrenal gland). There is also an AT2 receptor found in many tissues but it is not known to be associated with cardiovascular homeostasis. Neither losartan nor its principal active metabolite exhibits any partial agonist activity at the AT1 receptor, and both have much greater affinity (about 1000-fold) for the AT1 receptor than for the AT2 receptor. In vitro binding studies indicate that losartan is a reversible, competitive inhibitor of the AT1 receptor. The active metabolite is 10 to 40 times more potent by weight than losartan and appears to be a reversible, non-competitive inhibitor of the AT1 receptor.

Neither losartan nor its active metabolite inhibits ACE (kininase II, the enzyme that converts angiotensin I to angiotensin II and degrades bradykinin), nor do they bind to or block other hormone receptors or ion channels known to be important in cardiovascular regulation.

12.2 Pharmacodynamics

Losartan inhibits the pressor effect of angiotensin II (as well as angiotensin I) infusions. A dose of 100 mg inhibits the pressor effect by about 85% at peak with 25-40% inhibition persisting for 24 hours. Removal of the negative feedback of angiotensin II causes a doubling to tripling in plasma renin activity and consequent rise in angiotensin II plasma concentration in hypertensive patients. Losartan does not affect the response to bradykinin, whereas ACE inhibitors increase the response to bradykinin. Aldosterone plasma concentrations fall following losartan administration. In spite of the effect of losartan on aldosterone secretion, very little effect on serum potassium was observed.

The effect of losartan is substantially present within one week but in some studies the maximal effect occurred in 3-6 weeks. In long-term follow-up studies (without placebo control) the effect of losartan appeared to be maintained for up to a year. There is no apparent rebound effect after abrupt withdrawal of losartan. There was essentially no change in average heart rate in losartan-treated patients in controlled trials.

12.3 Pharmacokinetics

Absorption: Following oral administration, losartan is well absorbed and undergoes substantial first-pass metabolism. The systemic bioavailability of losartan is approximately 33%. Mean peak concentrations of losartan and its active metabolite are reached in 1 hour and in 3-4 hours, respectively. While maximum plasma concentrations of losartan and its active metabolite are approximately equal, the AUC (area under the curve) of the metabolite is about 4 times as great as that of losartan. A meal slows absorption of losartan and decreases its Cmax but has only minor effects on losartan AUC or on the AUC of the metabolite (~10% decrease). The pharmacokinetics of losartan and its active metabolite are linear with oral losartan doses up to 200 mg and do not change over time.

Distribution: The volume of distribution of losartan and the active metabolite is about 34 liters and 12 liters, respectively. Both losartan and its active metabolite are highly bound to plasma proteins, primarily albumin, with plasma free fractions of 1.3% and 0.2%, respectively. Plasma protein binding is constant over the concentration range achieved with recommended doses. Studies in rats indicate that losartan crosses the blood-brain barrier poorly, if at all.

Metabolism: Losartan is an orally active agent that undergoes substantial first-pass metabolism by cytochrome P450 enzymes. It is converted, in part, to an active carboxylic acid metabolite that is responsible for most of the angiotensin II receptor antagonism that follows losartan treatment. About 14% of an orally-administered dose of losartan is converted to the active metabolite. In addition to the active carboxylic acid metabolite, several inactive metabolites are formed. In vitro studies indicate that cytochrome P450 2C9 and 3A4 are involved in the biotransformation of losartan to its metabolites.

Elimination: Total plasma clearance of losartan and the active metabolite is about 600 mL/min and 50 mL/min, respectively, with renal clearance of about 75 mL/min and 25 mL/min, respectively. The terminal half-life of losartan is about 2 hours and of the metabolite is about 6-9 hours. After single doses of losartan administered orally, about 4% of the dose is excreted unchanged in the urine and about 6% is excreted in urine as active metabolite. Biliary excretion contributes to the elimination of losartan and its metabolites. Following oral ^14C-labeled losartan, about 35% of radioactivity is recovered in the urine and about 60% in the feces. Following an intravenous dose of ^14C-labeled losartan, about 45% of radioactivity is recovered in the urine and 50% in the feces. Neither losartan nor its metabolite accumulates in plasma upon repeated once-daily dosing.

Specific Populations

Pediatric: Pharmacokinetic parameters after multiple doses of losartan (average dose 0.7 mg/kg, range 0.36 to 0.97 mg/kg) as a tablet to 25 hypertensive patients aged 6 to 16 years are shown in Table 4 below. Pharmacokinetics of losartan and its active metabolite were generally similar across the studied age groups and similar to historical pharmacokinetic data in adults. The principal pharmacokinetic parameters in adults and children are shown in the table below.

Table 2: Pharmacokinetic Parameters in Hypertensive Adults and Children Age 6-16 Following Multiple Dosing

 | Adults given 50 mg once daily for 7 days N=12 |  | Age 6-16 given 0.7 mg/kg once daily for 7 days N=25
 | Parent | Active Metabolite | Parent | Active Metabolite
AUC0-24 (ng∙hr/mL) [Mean ± standard deviation] | 442 ± 173 | 1685 ± 452 | 368 ± 169 | 1866 ± 1076
CMAX (ng/mL) | 224 ± 82 | 212 ± 73 | 141 ± 88 | 222 ± 127
T1/2 (h) [Harmonic mean and standard deviation] | 2.1 ± 0.70 | 7.4 ± 2.4 | 2.3 ± 0.8 | 5.6 ± 1.2
TPEAK (h) [Median] | 0.9 | 3.5 | 2.0 | 4.1
CLREN (mL/min) | 56 ± 23 | 20 ± 3 | 53 ± 33 | 17 ± 8

The bioavailability of the suspension formulation was compared with losartan tablets in healthy adults. The suspension and tablet are similar in their bioavailability with respect to both losartan and the active metabolite [see Dosage and Administration (2.5)].

Geriatric and Gender: Losartan pharmacokinetics have been investigated in the elderly (65-75 years) and in both genders. Plasma concentrations of losartan and its active metabolite are similar in elderly and young hypertensives. Plasma concentrations of losartan were about twice as high in female hypertensives as male hypertensives, but concentrations of the active metabolite were similar in males and females. No dosage adjustment is necessary [see Dosage and Administration (2.1)].

Race: Pharmacokinetic differences due to race have not been studied [see Use in Specific Populations (8.6)].

Renal Insufficiency: Following oral administration, plasma concentrations and AUCs of losartan and its active metabolite are increased by 50-90% in patients with mild (creatinine clearance of 50 to 74 mL/min) or moderate (creatinine clearance 30 to 49 mL/min) renal insufficiency. In this study, renal clearance was reduced by 55-85% for both losartan and its active metabolite in patients with mild or moderate renal insufficiency. Neither losartan nor its active metabolite can be removed by hemodialysis [see Warnings and Precautions (5.3) and Use in Specific Populations (8.7)].

Hepatic Insufficiency: Following oral administration in patients with mild to moderate alcoholic cirrhosis of the liver, plasma concentrations of losartan and its active metabolite were, respectively, 5-times and about 1.7-times those in young male volunteers. Compared to normal subjects the total plasma clearance of losartan in patients with hepatic insufficiency was about 50% lower and the oral bioavailability was about doubled. Use a starting dose of 25 mg for patients with mild to moderate hepatic impairment. COZAAR has not been studied in patients with severe hepatic impairment [see Dosage and Administration (2.4) and Use in Specific Populations (8.8)].

Drug Interactions

No clinically significant drug interactions have been found in studies of losartan potassium with hydrochlorothiazide, digoxin, warfarin, cimetidine and phenobarbital. However, rifampin has been shown to decrease the AUC of losartan and its active metabolite by 30% and 40%, respectively. Fluconazole, an inhibitor of cytochrome P450 2C9, decreased the AUC of the active metabolite by approximately 40%, but increased the AUC of losartan by approximately 70% following multiple doses. Conversion of losartan to its active metabolite after intravenous administration is not affected by ketoconazole, an inhibitor of P450 3A4. The AUC of active metabolite following oral losartan was not affected by erythromycin, an inhibitor of P450 3A4, but the AUC of losartan was increased by 30%.

The pharmacodynamic consequences of concomitant use of losartan and inhibitors of P450 2C9 have not been examined. Subjects who do not metabolize losartan to active metabolite have been shown to have a specific, rare defect in cytochrome P450 2C9. These data suggest that the conversion of losartan to its active metabolite is mediated primarily by P450 2C9 and not P450 3A4.

13 NONCLINICAL TOXICOLOGY

13.1 Carcinogenesis, Mutagenesis, Impairment of Fertility

Losartan potassium was not carcinogenic when administered at maximally tolerated dosages to rats and mice for 105 and 92 weeks, respectively. Female rats given the highest dose (270 mg/kg/day) had a slightly higher incidence of pancreatic acinar adenoma. The maximally tolerated dosages (270 mg/kg/day in rats, 200 mg/kg/day in mice) provided systemic exposures for losartan and its pharmacologically active metabolite that were approximately 160 and 90 times (rats) and 30 and 15 times (mice) the exposure of a 50 kg human given 100 mg per day.

Losartan potassium was negative in the microbial mutagenesis and V-79 mammalian cell mutagenesis assays and in the in vitro alkaline elution and in vitro and in vivo chromosomal aberration assays. In addition, the active metabolite showed no evidence of genotoxicity in the microbial mutagenesis, in vitro alkaline elution, and in vitro chromosomal aberration assays.

Fertility and reproductive performance were not affected in studies with male rats given oral doses of losartan potassium up to approximately 150 mg/kg/day. The administration of toxic dosage levels in females (300/200 mg/kg/day) was associated with a significant (p<0.05) decrease in the number of corpora lutea/female, implants/female, and live fetuses/female at C-section. At 100 mg/kg/day only a decrease in the number of corpora lutea/female was observed. The relationship of these findings to drug-treatment is uncertain since there was no effect at these dosage levels on implants/pregnant female, percent post-implantation loss, or live animals/litter at parturition. In nonpregnant rats dosed at 135 mg/kg/day for 7 days, systemic exposure (AUCs) for losartan and its active metabolite were approximately 66 and 26 times the exposure achieved in man at the maximum recommended human daily dosage (100 mg).

14 CLINICAL STUDIES

14.1 Hypertension

Adult Hypertension

The antihypertensive effects of COZAAR were demonstrated principally in 4 placebo-controlled, 6- to 12-week trials of dosages from 10 to 150 mg per day in patients with baseline diastolic blood pressures of 95-115. The studies allowed comparisons of two doses (50-100 mg/day) as once-daily or twice-daily regimens, comparisons of peak and trough effects, and comparisons of response by gender, age, and race. Three additional studies examined the antihypertensive effects of losartan and hydrochlorothiazide in combination.

The 4 studies of losartan monotherapy included a total of 1075 patients randomized to several doses of losartan and 334 to placebo. The 10- and 25-mg doses produced some effect at peak (6 hours after dosing) but small and inconsistent trough (24 hour) responses. Doses of 50, 100 and 150 mg once daily gave statistically significant systolic/diastolic mean decreases in blood pressure, compared to placebo in the range of 5.5-10.5/3.5-7.5 mmHg, with the 150-mg dose giving no greater effect than 50-100 mg. Twice-daily dosing at 50-100 mg/day gave consistently larger trough responses than once-daily dosing at the same total dose. Peak (6 hour) effects were uniformly, but moderately, larger than trough effects, with the trough-to-peak ratio for systolic and diastolic responses 50-95% and 60-90%, respectively.

Addition of a low dose of hydrochlorothiazide (12.5 mg) to losartan 50 mg once daily resulted in placebo-adjusted blood pressure reductions of 15.5/9.2 mmHg.

Analysis of age, gender, and race subgroups of patients showed that men and women, and patients over and under 65, had generally similar responses. COZAAR was effective in reducing blood pressure regardless of race, although the effect was somewhat less in Black patients (usually a low-renin population).

Pediatric Hypertension

The antihypertensive effect of losartan was studied in one trial enrolling 177 hypertensive pediatric patients aged 6 to 16 years old. Children who weighed <50 kg received 2.5, 25 or 50 mg of losartan daily and patients who weighed ≥50 kg received 5, 50 or 100 mg of losartan daily. Children in the lowest dose group were given losartan in a suspension formulation [see Dosage and Administration (2.1)]. The majority of the children had hypertension associated with renal and urogenital disease. The sitting diastolic blood pressure (SiDBP) on entry into the study was higher than the 95th percentile level for the patient's age, gender, and height. At the end of three weeks, losartan reduced systolic and diastolic blood pressure, measured at trough, in a dose-dependent manner. Overall, the two higher doses (25 to 50 mg in patients <50 kg; 50 to 100 mg in patients ≥50 kg) reduced diastolic blood pressure by 5 to 6 mmHg more than the lowest dose used (2.5 mg in patients <50 kg; 5 mg in patients ≥50 kg). The lowest dose, corresponding to an average daily dose of 0.07 mg/kg, did not appear to offer consistent antihypertensive efficacy. When patients were randomized to continue losartan at the two higher doses or to placebo after 3 weeks of therapy, trough diastolic blood pressure rose in patients on placebo between 5 and 7 mmHg more than patients randomized to continuing losartan. When the low dose of losartan was randomly withdrawn, the rise in trough diastolic blood pressure was the same in patients receiving placebo and in those continuing losartan, again suggesting that the lowest dose did not have significant antihypertensive efficacy. Overall, no significant differences in the overall antihypertensive effect of losartan were detected when the patients were analyzed according to age (<, ≥12 years old) or gender. While blood pressure was reduced in all racial subgroups examined, too few non-White patients were enrolled to compare the dose-response of losartan in the non-White subgroup.

14.2 Hypertensive Patients with Left Ventricular Hypertrophy

The LIFE study was a multinational, double-blind study comparing COZAAR and atenolol in 9193 hypertensive patients with ECG-documented left ventricular hypertrophy. Patients with myocardial infarction or stroke within six months prior to randomization were excluded. Patients were randomized to receive once daily COZAAR 50 mg or atenolol 50 mg. If goal blood pressure (<140/90 mmHg) was not reached, hydrochlorothiazide (12.5 mg) was added first and, if needed, the dose of COZAAR or atenolol was then increased to 100 mg once daily. If necessary, other antihypertensive treatments (e.g., increase in dose of hydrochlorothiazide therapy to 25 mg or addition of other diuretic therapy, calcium-channel blockers, alpha-blockers, or centrally acting agents, but not ACE inhibitors, angiotensin II antagonists, or beta-blockers) were added to the treatment regimen to reach the goal blood pressure.

Of the randomized patients, 4963 (54%) were female and 533 (6%) were Black. The mean age was 67 with 5704 (62%) age ≥65. At baseline, 1195 (13%) had diabetes, 1326 (14%) had isolated systolic hypertension, 1469 (16%) had coronary heart disease, and 728 (8%) had cerebrovascular disease. Baseline mean blood pressure was 174/98 mmHg in both treatment groups. The mean length of follow-up was 4.8 years. At the end of study or at the last visit before a primary endpoint, 77% of the group treated with COZAAR and 73% of the group treated with atenolol were still taking study medication. Of the patients still taking study medication, the mean doses of COZAAR and atenolol were both about 80 mg/day, and 15% were taking atenolol or losartan as monotherapy, while 77% were also receiving hydrochlorothiazide (at a mean dose of 20 mg/day in each group). Blood pressure reduction measured at trough was similar for both treatment groups but blood pressure was not measured at any other time of the day. At the end of study or at the last visit before a primary endpoint, the mean blood pressures were 144.1/81.3 mmHg for the group treated with COZAAR and 145.4/80.9 mmHg for the group treated with atenolol; the difference in systolic blood pressure (SBP) of 1.3 mmHg was significant (p<0.001), while the difference of 0.4 mmHg in diastolic blood pressure (DBP) was not significant (p=0.098).

The primary endpoint was the first occurrence of cardiovascular death, nonfatal stroke, or nonfatal myocardial infarction. Patients with nonfatal events remained in the trial, so that there was also an examination of the first event of each type even if it was not the first event (e.g., a stroke following an initial myocardial infarction would be counted in the analysis of stroke). Treatment with COZAAR resulted in a 13% reduction (p=0.021) in risk of the primary endpoint compared to the atenolol group (see Figure 1 and Table 3); this difference was primarily the result of an effect on fatal and nonfatal stroke. Treatment with COZAAR reduced the risk of stroke by 25% relative to atenolol (p=0.001) (see Figure 2 and Table 3).

Figure 1: Kaplan-Meier estimates of the primary endpoint of time to cardiovascular death, nonfatal stroke, or nonfatal myocardial infarction in the groups treated with COZAAR and atenolol. The Risk Reduction is adjusted for baseline Framingham risk score and level of electrocardiographic left ventricular hypertrophy.

Figure 2: Kaplan-Meier estimates of the time to fatal/nonfatal stroke in the groups treated with COZAAR and atenolol. The Risk Reduction is adjusted for baseline Framingham risk score and level of electrocardiographic left ventricular hypertrophy.

Table 3 shows the results for the primary composite endpoint and the individual endpoints. The primary endpoint was the first occurrence of stroke, myocardial infarction or cardiovascular death, analyzed using an ITT approach. The table shows the number of events for each component in two different ways. The Components of Primary Endpoint (as a first event) counts only the events that define the primary endpoint, while the Secondary Endpoints count all first events of a particular type, whether or not they were preceded by a different type of event.

Table 3: Incidence of Primary Endpoint Events
 | COZAAR |  | Atenolol |  | Risk Reduction [Adjusted for baseline Framingham risk score and level of electrocardiographic left ventricular hypertrophy] | 95% CI | p-Value
 | N (%) | Rate [Rate per 1000 patient-years of follow-up] | N (%) | Rate
Primary Composite Endpoint | 508 (11) | 23.8 | 588 (13) | 27.9 | 13% | 2% to 23% | 0.021
Components of Primary Composite Endpoint (as a first event)
Stroke (nonfatal) | 209 (5) |  | 286 (6)
Myocardial infarction (nonfatal) | 174 (4) |  | 168 (4)
Cardiovascular mortality | 125 (3) |  | 134 (3)
Secondary Endpoints (any time in study)
Stroke (fatal/nonfatal) | 232 (5) | 10.8 | 309 (7) | 14.5 | 25% | 11% to 37% | 0.001
Myocardial infarction (fatal/nonfatal) | 198 (4) | 9.2 | 188 (4) | 8.7 | -7% | -13% to 12% | 0.491
Cardiovascular mortality | 204 (4) | 9.2 | 234 (5) | 10.6 | 11% | -7% to 27% | 0.206
Due to CHD | 125 (3) | 5.6 | 124 (3) | 5.6 | -3% | -32% to 20% | 0.839
Due to Stroke | 40 (1) | 1.8 | 62 (1) | 2.8 | 35% | 4% to 67% | 0.032
Other [Death due to heart failure, non-coronary vascular disease, pulmonary embolism, or a cardiovascular cause other than stroke or coronary heart disease] | 39 (1) | 1.8 | 48 (1) | 2.2 | 16% | -28% to 45% | 0.411

Although the LIFE study favored COZAAR over atenolol with respect to the primary endpoint (p=0.021), this result is from a single study and, therefore, is less compelling than the difference between COZAAR and placebo. Although not measured directly, the difference between COZAAR and placebo is compelling because there is evidence that atenolol is itself effective (vs. placebo) in reducing cardiovascular events, including stroke, in hypertensive patients.

Other clinical endpoints of the LIFE study were: total mortality, hospitalization for heart failure or angina pectoris, coronary or peripheral revascularization procedures, and resuscitated cardiac arrest. There were no significant differences in the rates of these endpoints between the COZAAR and atenolol groups.

For the primary endpoint and stroke, the effects of COZAAR in patient subgroups defined by age, gender, race and presence or absence of isolated systolic hypertension (ISH), diabetes, and history of cardiovascular disease (CVD) are shown in Figure 3 below. Subgroup analyses can be difficult to interpret and it is not known whether these represent true differences or chance effects.

Figure 3: Primary Endpoint Events† within Demographic Subgroups

14.3 Nephropathy in Type 2 Diabetic Patients

The RENAAL study was a randomized, placebo-controlled, double-blind, multicenter study conducted worldwide in 1513 patients with type 2 diabetes with nephropathy (defined as serum creatinine 1.3 to 3.0 mg/dL in females or males ≤60 kg and 1.5 to 3.0 mg/dL in males >60 kg and proteinuria [urinary albumin to creatinine ratio ≥300 mg/g]).

Patients were randomized to receive COZAAR 50 mg once daily or placebo on a background of conventional antihypertensive therapy excluding ACE inhibitors and angiotensin II antagonists. After one month, investigators were instructed to titrate study drug to 100 mg once daily if the trough blood pressure goal (140/90 mmHg) was not achieved. Overall, 72% of patients received the 100-mg daily dose more than 50% of the time they were on study drug. Because the study was designed to achieve equal blood pressure control in both groups, other antihypertensive agents (diuretics, calcium-channel blockers, alpha- or beta-blockers, and centrally acting agents) could be added as needed in both groups. Patients were followed for a mean duration of 3.4 years.

The study population was diverse with regard to race (Asian 16.7%, Black 15.2%, Hispanic 18.3%, White 48.6%). Overall, 63.2% of the patients were men, and 66.4% were under the age of 65 years. Almost all of the patients (96.6%) had a history of hypertension, and the patients entered the trial with a mean serum creatinine of 1.9 mg/dL and mean proteinuria (urinary albumin/creatinine) of 1808 mg/g at baseline.

The primary endpoint of the study was the time to first occurrence of any one of the following events: doubling of serum creatinine, end-stage renal disease (ESRD) (need for dialysis or transplantation), or death. Treatment with COZAAR resulted in a 16% risk reduction in this endpoint (see Figure 4 and Table 4). Treatment with COZAAR also reduced the occurrence of sustained doubling of serum creatinine by 25% and ESRD by 29% as separate endpoints, but had no effect on overall mortality (see Table 4).

The mean baseline blood pressures were 152/82 mmHg for COZAAR plus conventional antihypertensive therapy and 153/82 mmHg for placebo plus conventional antihypertensive therapy. At the end of the study, the mean blood pressures were 143/76 mmHg for the group treated with COZAAR and 146/77 mmHg for the group treated with placebo.

Figure 4: Kaplan-Meier curve for the primary composite endpoint of doubling of serum creatinine, end stage renal disease (need for dialysis or transplantation) or death.

Table 4: Incidence of Primary Endpoint Events
 | Incidence |  | Risk Reduction | 95% C.I. | p-Value
 | Losartan | Placebo
Primary Composite Endpoint | 43.5% | 47.1% | 16.1% | 2.3% to 27.9% | 0.022
Doubling of Serum Creatinine, ESRD and Death Occurring as a First Event
Doubling of Serum Creatinine | 21.6% | 26.0%
ESRD | 8.5% | 8.5%
Death | 13.4% | 12.6%
Overall Incidence of Doubling of Serum Creatinine, ESRD and Death
Doubling of Serum Creatinine | 21.6% | 26.0% | 25.3% | 7.8% to 39.4% | 0.006
ESRD | 19.6% | 25.5% | 28.6% | 11.5% to 42.4% | 0.002
Death | 21.0% | 20.3% | -1.7% | -26.9% to 18.6% | 0.884

The secondary endpoints of the study were change in proteinuria, change in the rate of progression of renal disease, and the composite of morbidity and mortality from cardiovascular causes (hospitalization for heart failure, myocardial infarction, revascularization, stroke, hospitalization for unstable angina, or cardiovascular death). Compared with placebo, COZAAR significantly reduced proteinuria by an average of 34%, an effect that was evident within 3 months of starting therapy, and significantly reduced the rate of decline in glomerular filtration rate during the study by 13%, as measured by the reciprocal of the serum creatinine concentration. There was no significant difference in the incidence of the composite endpoint of cardiovascular morbidity and mortality.

The favorable effects of COZAAR were seen in patients also taking other anti-hypertensive medications (angiotensin II receptor antagonists and angiotensin converting enzyme inhibitors were not allowed), oral hypoglycemic agents and lipid-lowering agents.

For the primary endpoint and ESRD, the effects of COZAAR in patient subgroups defined by age, gender and race are shown in Table 5 below. Subgroup analyses can be difficult to interpret and it is not known whether these represent true differences or chance effects.

Table 5: Efficacy Outcomes within Demographic Subgroups
 |  | Primary Composite Endpoint |  |  | ESRD
 | No. of Patients | COZAAR Event Rate % | Placebo Event Rate % | Hazard Ratio (95% CI) | COZAAR Event Rate % | Placebo Event Rate % | Hazard Ratio (95% CI)
Overall Results | 1513 | 43.5 | 47.1 | 0.84 (0.72, 0.98) | 19.6 | 25.5 | 0.71 (0.58, 0.89)
Age
<65 years | 1005 | 44.1 | 49.0 | 0.78 (0.65, 0.94) | 21.1 | 28.5 | 0.67 (0.52, 0.86)
≥65 years | 508 | 42.3 | 43.5 | 0.98 (0.75, 1.28) | 16.5 | 19.6 | 0.85 (0.56, 1.28)
Gender
Female | 557 | 47.8 | 54.1 | 0.76 (0.60, 0.96) | 22.8 | 32.8 | 0.60 (0.44, 0.83)
Male | 956 | 40.9 | 43.3 | 0.89 (0.73, 1.09) | 17.5 | 21.5 | 0.81 (0.60, 1.08)
Race
Asian | 252 | 41.9 | 54.8 | 0.66 (0.45, 0.95) | 18.8 | 27.4 | 0.63 (0.37, 1.07)
Black | 230 | 40.0 | 39.0 | 0.98 (0.65, 1.50) | 17.6 | 21.0 | 0.83 (0.46, 1.52)
Hispanic | 277 | 55.0 | 54.0 | 1.00 (0.73, 1.38) | 30.0 | 28.5 | 1.02 (0.66, 1.59)
White | 735 | 40.5 | 43.2 | 0.81 (0.65, 1.01) | 16.2 | 23.9 | 0.60 (0.43, 0.83)

16 HOW SUPPLIED/STORAGE AND HANDLING

COZAAR is a white film-coated tablet supplied as follows:

Losartan | Shape | Engraving (reverse) | NDC 78206-xxx-xx
Losartan | Shape | Engraving (reverse) | Bottle/30 | Bottle/90
25 mg | oval | 951 | n/a | 121-01
50 mg | oval | 952 (scored) | 122-01 | 122-02
100 mg | teardrop | 960 | 123-01 | 123-02

STORAGE AND HANDLING

Store at 25°C (77°F); excursions permitted to 15-30°C (59-86°F) [see USP Controlled Room Temperature]. Keep container tightly closed. Protect from light.

17 PATIENT COUNSELING INFORMATION

Advise the patient to read the FDA-approved patient labeling (Patient Information).

Pregnancy

Advise female patients of childbearing age about the consequences of exposure to COZAAR during pregnancy. Discuss treatment options with women planning to become pregnant. Tell patients to report pregnancies to their physicians as soon as possible [see Warnings and Precautions (5.1) and Use in Specific Populations (8.1)].

Potassium Supplements

Advise patients receiving COZAAR not to use potassium supplements or salt substitutes containing potassium without consulting their healthcare provider [see Drug Interactions (7.1)].

Manufactured for: Organon LLC, a subsidiary of
ORGANON & Co.,
Jersey City, NJ 07302, USA

For patent information: www.organon.com/our-solutions/patent/

The trademarks depicted herein are owned by their respective companies.

© 2025 Organon group of companies. All rights reserved.

uspi-og0954-t-2506r002

Patient Information COZAAR® (CO-zar) (losartan potassium tablets) 25 mg, 50 mg, 100 mg Rx only

Read the Patient Information that comes with COZAAR® before you start taking it and each time you get a refill. There may be new information. This leaflet does not take the place of talking with your doctor about your condition and treatment.

What is the most important information I should know about COZAAR?

- COZAAR can cause harm or death to an unborn baby.
- Talk to your doctor about other ways to lower your blood pressure if you plan to become pregnant.
- If you get pregnant while taking COZAAR, tell your doctor right away.

What is COZAAR?

COZAAR is a prescription medicine called an angiotensin receptor blocker (ARB). It is used:

- alone or with other blood pressure medicines to lower high blood pressure (hypertension).
- to lower the chance of stroke in patients with high blood pressure and a heart problem called left ventricular hypertrophy. COZAAR may not help Black patients with this problem.
- to slow the worsening of diabetic kidney disease (nephropathy) in patients with type 2 diabetes who have or had high blood pressure.

COZAAR has not been studied in children less than 6 years old or in children with certain kidney problems.

High Blood Pressure (hypertension). Blood pressure is the force in your blood vessels when your heart beats and when your heart rests. You have high blood pressure when the force is too much. COZAAR can help your blood vessels relax so your blood pressure is lower.

Left Ventricular Hypertrophy (LVH) is an enlargement of the walls of the left chamber of the heart (the heart's main pumping chamber). LVH can happen from several things. High blood pressure is the most common cause of LVH.

Type 2 Diabetes with Nephropathy. Type 2 diabetes is a type of diabetes that happens mainly in adults. If you have diabetic nephropathy it means that your kidneys do not work properly because of damage from the diabetes.

Who should not take COZAAR?

- Do not take COZAAR if you are allergic to any of the ingredients in COZAAR. See the end of this leaflet for a complete list of ingredients in COZAAR.
- Do not take COZAAR if you have diabetes and are taking a medicine called aliskiren to reduce blood pressure.

What should I tell my doctor before taking COZAAR?

Tell your doctor about all of your medical conditions including if you:

- are pregnant or planning to become pregnant. See "What is the most important information I should know about COZAAR?"
- are breastfeeding. It is not known if COZAAR passes into your breast milk. You should choose either to take COZAAR or breastfeed, but not both.
- are vomiting a lot or having a lot of diarrhea
- have liver problems
- have kidney problems

Tell your doctor about all the medicines you take, including prescription and non-prescription medicines, vitamins, and herbal supplements. COZAAR and certain other medicines may interact with each other. Especially tell your doctor if you are taking:

- potassium supplements
- salt substitutes containing potassium
- other medicines that may increase serum potassium
- water pills (diuretics)
- lithium (a medicine used to treat a certain kind of depression)
- medicines used to treat pain and arthritis, called non-steroidal anti-inflammatory drugs (NSAIDs), including COX-2 inhibitors
- other medicines to reduce blood pressure

How should I take COZAAR?

- Take COZAAR exactly as prescribed by your doctor. Your doctor may change your dose if needed.
- COZAAR can be taken with or without food.
- If you miss a dose, take it as soon as you remember. If it is close to your next dose, do not take the missed dose. Just take the next dose at your regular time.
- If you take too much COZAAR, call your doctor or Poison Control Center, or go to the nearest hospital emergency room right away.

What are the possible side effects of COZAAR?

COZAAR may cause the following side effects that may be serious:

- Injury or death of unborn babies. See "What is the most important information I should know about COZAAR?"
- Allergic reaction. Symptoms of an allergic reaction are swelling of the face, lips, throat or tongue. Get emergency medical help right away and stop taking COZAAR.
- Low blood pressure (hypotension). Low blood pressure may cause you to feel faint or dizzy. Lie down if you feel faint or dizzy. Call your doctor right away.
- For people who already have kidney problems, you may see a worsening in how well your kidneys work. Call your doctor if you get swelling in your feet, ankles, or hands, or unexplained weight gain.
- High blood levels of potassium

The most common side effects of COZAAR in people with high blood pressure are:

- "colds" (upper respiratory infection)
- dizziness
- stuffy nose
- back pain

The most common side effects of COZAAR in people with type 2 diabetes with diabetic kidney disease are:

- diarrhea
- tiredness
- low blood sugar
- chest pain
- high blood potassium
- low blood pressure

Tell your doctor if you get any side effect that bothers you or that won't go away.

This is not a complete list of side effects. For a complete list, ask your doctor or pharmacist.

How do I store COZAAR?

- Store COZAAR tablets at 59°F to 86°F (15°C to 30°C).
- Keep COZAAR in a tightly closed container that protects the medicine from light.
- Keep COZAAR and all medicines out of the reach of children.

General information about COZAAR

Medicines are sometimes prescribed for conditions that are not mentioned in patient information leaflets. Do not use COZAAR for a condition for which it was not prescribed. Do not give COZAAR to other people, even if they have the same symptoms that you have. It may harm them.

This leaflet summarizes the most important information about COZAAR. If you would like more information, talk with your doctor. You can ask your pharmacist or doctor for information about COZAAR that is written for health professionals.

What are the ingredients in COZAAR?

Active ingredients: losartan potassium

Inactive ingredients:

microcrystalline cellulose, lactose hydrous, pregelatinized starch, magnesium stearate, hydroxypropyl cellulose, hypromellose, and titanium dioxide. COZAAR 25 mg, COZAAR 50 mg, and COZAAR 100 mg may also contain carnauba wax.

Manufactured for: Organon LLC, a subsidiary of
ORGANON & Co.,
Jersey City, NJ 07302, USA

For patent information: www.organon.com/our-solutions/patent/

Copyright © 2021 Organon Global Inc.
All rights reserved.

Revised: 6/2021

usppi-og0954-t-2106r000

PRINCIPAL DISPLAY PANEL - 25 mg Tablet Bottle Label

NDC 78206-121-01

Cozaar®
(Losartan Potassium
Tablets)

25 mg

Each tablet contains 25 mg of losartan potassium.
Store at 25°C (77°F); excursions permitted to 15-30°C
(59-86°F) [see USP Controlled Room Temperature].
Keep container tightly closed.
Protect from light.

Rx only

90 Tablets

PRINCIPAL DISPLAY PANEL - 50 mg Tablet Bottle Label

NDC 78206-122-02

Cozaar®
(Losartan Potassium
Tablets)

50 mg

Each tablet contains 50 mg of losartan potassium.
Store at 25°C (77°F); excursions permitted to 15-30°C
(59-86°F) [see USP Controlled Room Temperature].
Keep container tightly closed.
Protect from light.

Rx only

90 Tablets

PRINCIPAL DISPLAY PANEL - 100 mg Tablet Bottle Label

NDC 78206-123-02

Cozaar®
(Losartan Potassium
Tablets)

100 mg

Each tablet contains 100 mg of losartan potassium.
Store at 25°C (77°F); excursions permitted to 15-30°C
(59-86°F) [see USP Controlled Room Temperature].
Keep container tightly closed.
Protect from light.

Rx only

90 Tablets